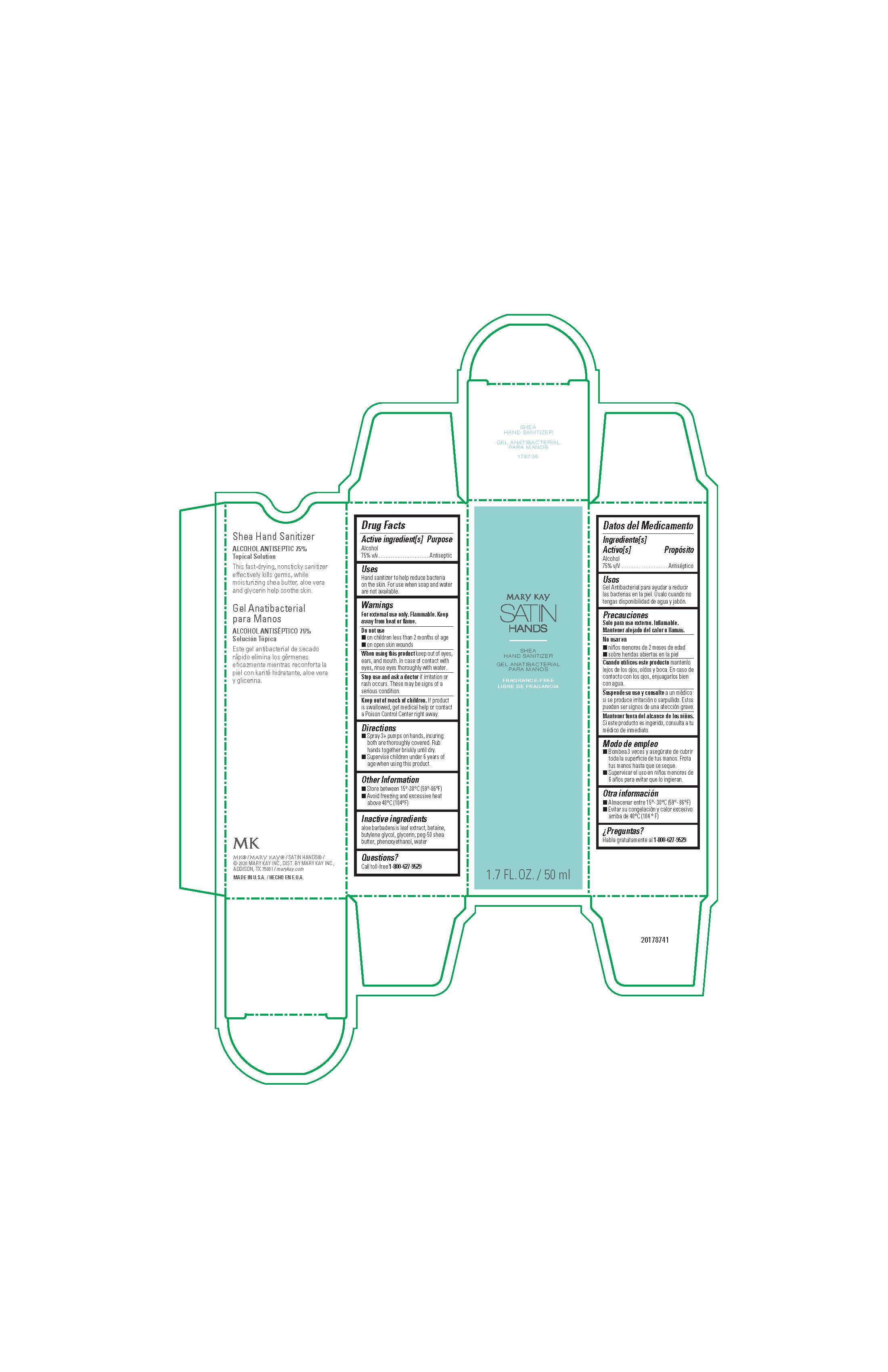 DRUG LABEL: Mary Kay Satin Hands Shea Hand Sanitizer
NDC: 51531-8735 | Form: SOLUTION
Manufacturer: Mary Kay Inc.
Category: otc | Type: HUMAN OTC DRUG LABEL
Date: 20241217

ACTIVE INGREDIENTS: ALCOHOL 75 mL/100 mL
INACTIVE INGREDIENTS: BETAINE; WATER; PHENOXYETHANOL; GLYCERIN; PEG-50 SHEA BUTTER; BUTYLENE GLYCOL; ALOE VERA LEAF

Mary Kay Satin Hands Shea Hand Sanitizer
Drug Facts

Active ingredient(s)

Alcohol 75% v/v

Purpose

Antiseptic

Uses

Hand sanitizer to help reduce bacteria
on the skin. For use when soap and water
are not available.

Warnings

For external use only. Flammable. Keep
away from heat or flame.

Do not use

- on children less than 2 months of age
- on open skin wounds

When using this product

keep out of eyes, ears, and mouth.

In case of contact with eyes, rinse eyes thoroughly with water.

Stop use and ask a doctor

if irritation or rash occurs.

These may be signs of a serious condition.

Keep out of reach of children.

If product is swallowed, get medical help or contact
a Poison Control Center right away.

Directions

- Spray 3+ pumps on hands, insuring both are thoroughly covered. Rub hands together briskly until dry.
- Supervise children under 6 years of age when using this product.

Other information

- Store between 15°-30°C (59°-86°F)
- Avoid freezing and excessive heat above 40°C (104°F)

Inactive ingredients

aloe barbadensis leaf extract, betaine,
butylene glycol, glycerin, peg-50 shea
butter, phenoxyethanol, water

Questions?

Call toll-free 1-800-627-9529

Principal Display Panel - 50 ml carton

Mary Kay

Satin Hands Shea Hand Sanitizer

Fragrance-Free

1.7 FL. OZ. / 50 ml